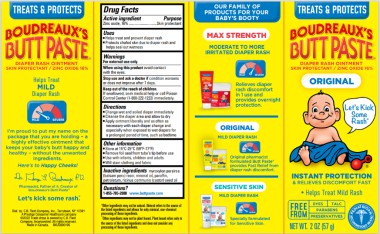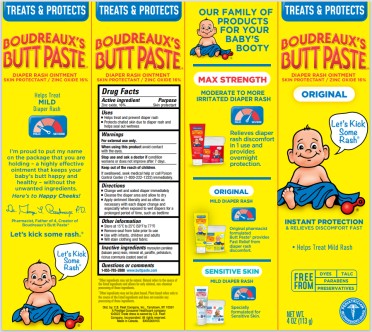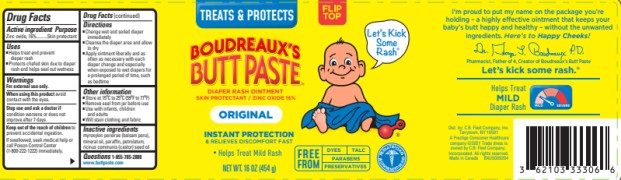 DRUG LABEL: Boudreauxs
NDC: 0132-0333 | Form: CREAM
Manufacturer: C.B. Fleet Company, Inc.
Category: otc | Type: HUMAN OTC DRUG LABEL
Date: 20251126

ACTIVE INGREDIENTS: ZINC OXIDE 16 g/113 g
INACTIVE INGREDIENTS: CASTOR OIL; MINERAL OIL; PARAFFIN; BALSAM PERU; PETROLATUM

Boudreauxs Butt Paste Original

Drug Facts

Active ingredient

Zinc oxide, 16%

Purpose

Skin protectant

Uses

- Helps treat and prevent diaper rash
- Protects chafed skin due to diaper rash and helps seal out wetness

Warnings

For external use only.

When using this product

avoid contact with the eyes.

Stop use and ask a doctor if

condition worsens or does not improve after 7 days.

Keep out of the reach of children

If swallowed, seek medical help or call Poison Control Center (1-800-222-1222) immediately.

Directions

- Change wet and soiled diaper immediately
- Cleanse the diaper area and allow to dry
- Apply ointment liberally and as often as necessary with each diaper change and especially when exposed to wet diapers for a prolonged period of time, such as bedtime

Other information

- Store at 15°C to 25°C (59°F to 77°F)
- Remove foil seal from the tube’s tip before use
- Use with infants, children and adults
- Will stain clothing and fabric

Inactive ingredients

myroxylon pereirae (balsam peru) resin, mineral oil, paraffin, petrolatum, ricinus communis (castor) seed oil

Questions or comments

1-855-785-2888 www.buttpaste.com

Principal display panel

BOUDREAUX’S® BUTT PASTE

Diaper Rash Ointment

Skin Protectant / Zinc Oxide 16%

Original

NET WT. 2 oz (57 g)

Principal display panel

BOUDREAUX’S® BUTT PASTE

Diaper Rash Ointment

Skin Protectant / Zinc Oxide 16%

Original

NET WT. 4 oz (113 g)

Principal display panel

BOUDREAUX’S® BUTT PASTE

Diaper Rash Ointment

Skin Protectant / Zinc Oxide 16%

Original

NET WT. 16 oz (1454 g)